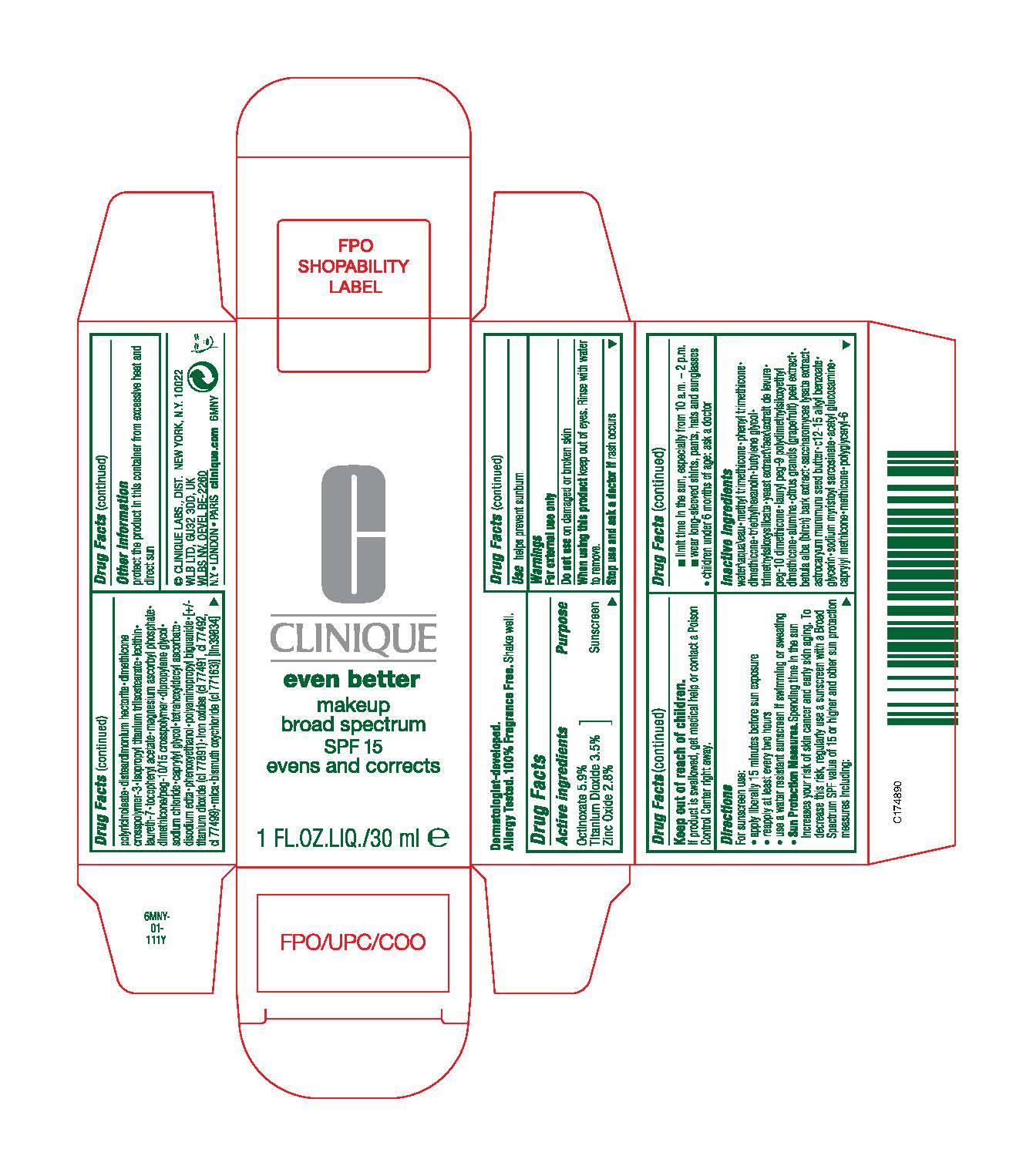 DRUG LABEL: EVEN BETTER MAKEUP
NDC: 49527-025 | Form: LIQUID
Manufacturer: CLINIQUE LABORATORIES LLC
Category: otc | Type: HUMAN OTC DRUG LABEL
Date: 20240109

ACTIVE INGREDIENTS: OCTINOXATE 59 mg/1 mL; TITANIUM DIOXIDE 35 mg/1 mL; ZINC OXIDE 28 mg/1 mL
INACTIVE INGREDIENTS: METHYL TRIMETHICONE; PHENYL TRIMETHICONE; DIMETHICONE; TRIETHYLHEXANOIN; BUTYLENE GLYCOL; YEAST, UNSPECIFIED; ALUMINUM OXIDE; CITRUS MAXIMA FRUIT RIND; BETULA PUBESCENS BARK; SACCHAROMYCES LYSATE; ASTROCARYUM MURUMURU SEED BUTTER; ALKYL (C12-15) BENZOATE; GLYCERIN; SODIUM MYRISTOYL SARCOSINATE; N-ACETYLGLUCOSAMINE; CAPRYLYL TRISILOXANE; ISOPROPYL TITANIUM TRIISOSTEARATE; LAURETH-7; .ALPHA.-TOCOPHEROL ACETATE; MAGNESIUM ASCORBYL PHOSPHATE; DIPROPYLENE GLYCOL; SODIUM CHLORIDE; CAPRYLYL GLYCOL; TETRAHEXYLDECYL ASCORBATE; EDETATE DISODIUM; PHENOXYETHANOL; POLIHEXANIDE; FERRIC OXIDE RED; FERRIC OXIDE YELLOW; FERROSOFERRIC OXIDE; MICA; BISMUTH OXYCHLORIDE; WATER

EVEN BETTER MAKEUP
BROAD SPECTRUM SPF 15

Drug Facts

Active ingredients

Octinoxate 5.9%
Titanium Dioxide 3.5%
Zinc Oxide 2.8%

Purpose

Sunscreen

Use

helps prevent sunburn

Warnings

For external use only

Do not use on damaged or broken skin

When using this product keep out of eyes. Rinse with water to remove.

Stop use and ask a doctor if rash occurs

Keep out of reach of children.

If product is swallowed, get medical help or contact a Poison Control Center right away.

Directions

For sunscreen use:

- apply liberally 15 minutes before sun exposure
- reapply at least every two hours
- use a water resistant sunscreen if swimming or sweating
- Sun Protection Measures. Spending time in the sun increases your risk of skin cancer and early skin aging. To decrease this risk, regularly use a sunscreen with a Broad Spectrum SPF value of 15 or higher and other sun protection measures including:
  - limit time in the sun, especially from 10 a.m. - 2 p.m.
  - wear long-sleeved shirts, pants, hats and sunglasses
- children under 6 months of age: ask a doctor

Inactive ingredients

water\aqua\eau • methyl trimethicone • phenyl trimethicone • dimethicone • triethylhexanoin • butylene glycol • trimethylsiloxysilicate • yeast extract\faex\extrait de levure • peg-10 dimethicone • lauryl peg-9 polydimethylsiloxyethyl dimethicone • alumina • citrus grandis (grapefruit) peel extract • betula alba (birch) bark extract • saccharomyces lysate extract • astrocaryum murumuru seed butter • c12-15 alkyl benzoate • glycerin • sodium myristoyl sarcosinate • acetyl glucosamine • caprylyl methicone • methicone • polyglyceryl-6 polyricinoleate • disteardimonium hectorite • dimethicone crosspolymer-3 • isopropyl titanium triisostearate • lecithin • laureth-7 • tocopheryl acetate • magnesium ascorbyl phosphate • dimethicone/peg-10/15 crosspolymer • dipropylene glycol • sodium chloride • caprylyl glycol • tetrahexyldecyl ascorbate • disodium edta • phenoxyethanol • polyaminopropyl biguanide • [+/- titanium dioxide (ci 77891) • iron oxides (ci 77491, ci 77492, ci 77499) • mica • bismuth oxychloride (ci 77163)] [iln39834]

Other information

protect the product in this container from excessive heat and direct sun

DIST.
NEW YORK, N.Y. 10022

PRINCIPAL DISPLAY PANEL - 30 ml Bottle Carton

C

CLINIQUE

even better

makeup
broad spectrum
SPF 15
evens and corrects

1 FL.OZ.LIQ./30 ml e